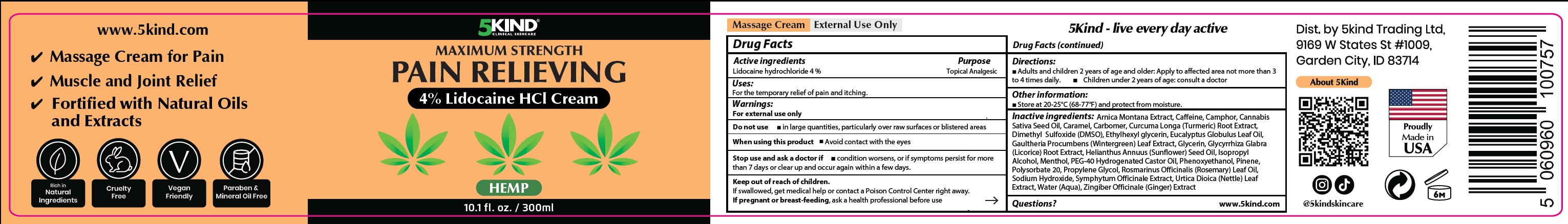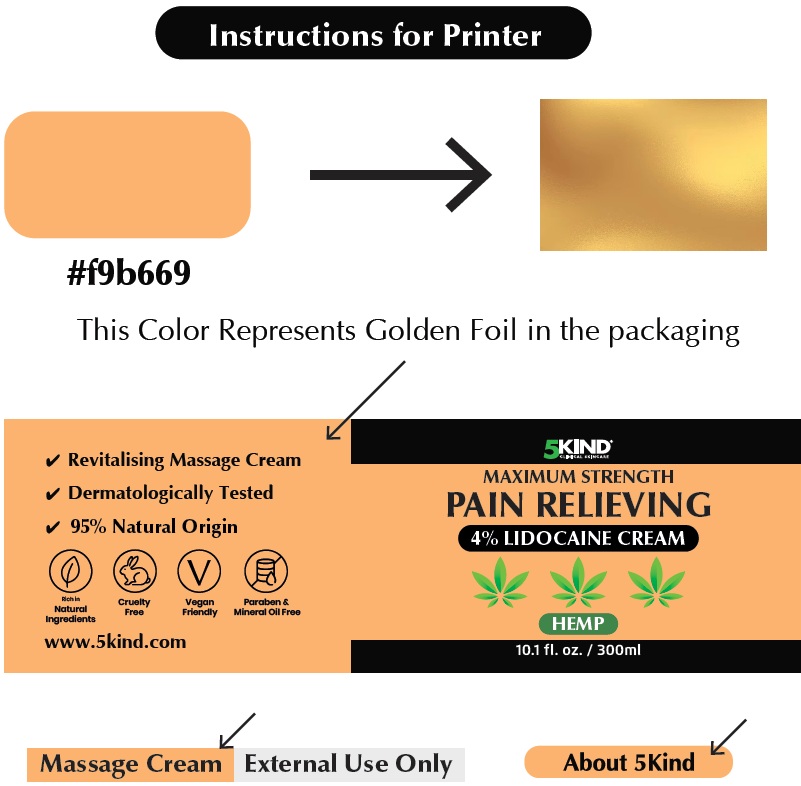 DRUG LABEL: 5Kind Maximum Strength Pain Relieving Lidocaine HCl Hemp
NDC: 85978-989 | Form: CREAM
Manufacturer: 5Kind Trading LTD
Category: otc | Type: HUMAN OTC DRUG LABEL
Date: 20260128

ACTIVE INGREDIENTS: LIDOCAINE HYDROCHLORIDE 40 mg/1 mL
INACTIVE INGREDIENTS: ARNICA MONTANA WHOLE; CAFFEINE; CANNABIS SATIVA SEED OIL; CARAMEL; CARBOMER HOMOPOLYMER, UNSPECIFIED TYPE; TURMERIC; DIMETHYL SULFOXIDE; ETHYLHEXYLGLYCERIN; EUCALYPTUS OIL; GAULTHERIA PROCUMBENS LEAF; GLYCERIN; GLYCYRRHIZA GLABRA (LICORICE) ROOT POWDER; SUNFLOWER OIL; ISOPROPYL ALCOHOL; MENTHOL; POLYOXYL 40 HYDROGENATED CASTOR OIL; PHENOXYETHANOL; PINENE; POLYSORBATE 20; PROPYLENE GLYCOL; ROSEMARY OIL; SODIUM HYDROXIDE; URTICA DIOICA LEAF; WATER; GINGER

5Kind Maximum Strength Pain Relieving 4% Lidocaine HCl Cream Hemp

Active ingredients

Lidocaine hydrochloride 4 %

Purpose

Topical Analgesic

Uses:

For the temporary relief of pain and itching.

Warnings:

For external use only

Do not use

- in large quantities, particularly over raw surfaces or blistered areas

When using this product

- Avoid contact with the eyes

Stop use and ask a doctor if

- condition worsens, or if symptoms persist for more than 7 days or clear up and occur again within a few days.

Keep out of reach of children.

If swallowed, get medical help or contact a Poison Control Center right away.

If pregnant or breast-feeding,

ask a health professional before use

Directions:

- Adults and children 2 years of age and older: Apply to affected area not more than 3 to 4 times daily.
- Children under 2 years of age: consult a doctor

Other information:

- Store at 20-25°C (68-77°F) and protect from moisture.

Inactive ingredients:

Arnica Montana Extract, Caffeine, Camphor, Cannabis Sativa Seed Oil, Caramel, Carbomer, Curcuma Longa (Turmeric) Root Extract, Dimethyl Sulfoxide (DMSO), Ethylhexyl glycerin, Eucalyptus Globulus Leaf Oil, Gaultheria Procumbens (Wintergreen) Leaf Extract, Glycerin, Glycyrrhiza Glabra (Licorice) Root Extract, Helianthus Annuus (Sunflower) Seed Oil, Isopropyl Alcohol, Menthol, PEG-40 Hydrogenated Castor Oil, Phenoxyethanol, Pinene, Polysorbate 20, Propylene Glycol, Rosmarinus Officinalis (Rosemary) Leaf Oil, Sodium Hydroxide, Symphytum Officinale Extract, Urtica Dioica (Nettle) Leaf Extract, Water (Aqua), Zingiber Officinale (Ginger) Extract

Questions?

www.5kind.com